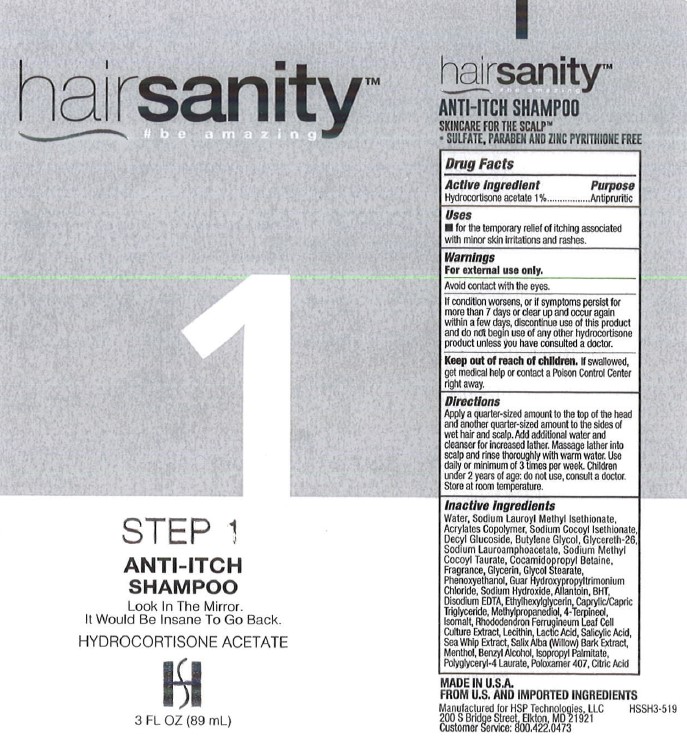 DRUG LABEL: H Plus Holdings
NDC: 58443-0412 | Form: SHAMPOO
Manufacturer: Prime Enterprises
Category: otc | Type: HUMAN OTC DRUG LABEL
Date: 20211026

ACTIVE INGREDIENTS: HYDROCORTISONE 10.2 mg/1 mL
INACTIVE INGREDIENTS: BENZYL ALCOHOL; CITRIC ACID MONOHYDRATE; ISOPROPYL PALMITATE; MENTHOL; WATER; BUTYLENE GLYCOL; COCAMIDOPROPYL BETAINE; DECYL GLUCOSIDE; LECITHIN, SOYBEAN; POLOXAMER 407; WILLOW BARK; PSEUDOPTEROGORGIA ELISABETHAE; SODIUM LAUROAMPHOACETATE; ETHYLHEXYLGLYCERIN; GLYCERETH-26; GLYCERIN; RHODODENDRON FERRUGINEUM LEAF; BUTYLATED HYDROXYTOLUENE; 4-TERPINEOL, (+/-)-; ALLANTOIN; METHYLPROPANEDIOL; SODIUM LAUROYL METHYL ISETHIONATE; PHENOXYETHANOL; SALICYLIC ACID; SODIUM COCOYL ISETHIONATE; SODIUM METHYL COCOYL TAURATE; LACTIC ACID; SODIUM HYDROXIDE; GLYCOL STEARATE; GUAR HYDROXYPROPYLTRIMONIUM CHLORIDE (1.7 SUBSTITUENTS PER SACCHARIDE); ISOMALT; MEDIUM-CHAIN TRIGLYCERIDES; EDETATE DISODIUM ANHYDROUS

H Plus 1.0% Hydrocortisone Nourishing Shampoo 3 Fl. Oz.

Active Ingredients

Hydrocortisone acetate 1%

Purpose

Antipuritic (Anti-Itch)

Uses

- for the temporary relief of itching associated with minor skin irritations and rashes.

Warnings

For external use only.

WHEN USING

Avoid contact wih the eyes.

ASK DOCTOR

If condition worsens, or if symptoms persist for more than 7 days or clear up and occur again within a few days, discontinue use of this product and do not begin use of any other hydrocortisone product unless you have consulted a doctor.

Keep out of reach of children. If swallowed, get medical help or contact a Posion Control Center right away.

Directions

Apply a quarter-sized amount to the top of the head and another quarter-sized amount to the sides of wet hair and scalp. Add additional water and cleanser for increased lather. Massage lather into scalp and rinse thoroughly with warm water. Use daily or minimum of 3 times per week. Children under 2 years of age: do not use, consult a doctor. Store at room temperature.

Inactive Ingredients

4-Terpineol, Acrylates Copolymer, Allantoin, Benzyl Alcohol, BHT, Butylene Glycol, Caprylic/Capric Triglyceride, Citric Acid, Cocamidopropyl Betaine, Decyl Glucoside, Disodium EDTA, Ethylhexylglycerin, Fragrance, Glycereth-26, Glycerin, Glycol Stearate, Guar Hydroxypropyltrimonium Chloride, Isomalt, Isopropyl Palmitate, Lactic Acid, Lecithin, Menthol, Methylpropanediol, Phenoxyethanol, Poloxamer 407, Polyglyceryl-4 Laurate, Rhododendron Ferrugineum Leaf Cell Culture Extract, Salicylic Acid, Salix Alba (Willow) Bark Extract, Sea Whip Extract, Sodium Cocoyl Isethionate, Sodium Hydroxide, Sodium Lauroamphoacetate, Sodium Lauroyl Methyl Isethionate, Sodium Methyl Cocoyl Taurate, Water